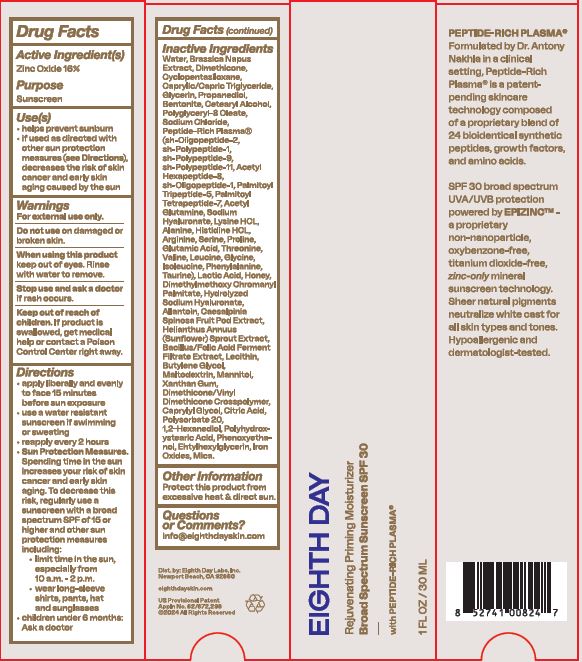 DRUG LABEL: Rejuvenating Priming Moisturizer BS Sunscreen SPF30
NDC: 62742-4258 | Form: CREAM
Manufacturer: Allure Labs
Category: otc | Type: HUMAN OTC DRUG LABEL
Date: 20240329

ACTIVE INGREDIENTS: ZINC OXIDE 16 g/100 g
INACTIVE INGREDIENTS: GLYCERIN; GLUTAMIC ACID; PHENOXYETHANOL; PROPANEDIOL; BRASSICA NAPUS WHOLE; HISTIDINE MONOHYDROCHLORIDE; PROLINE; PHENYLALANINE; SODIUM CHLORIDE; PALMITOYL TRIPEPTIDE-5; HYALURONATE SODIUM; ALLANTOIN; DIMETHICONE/VINYL DIMETHICONE CROSSPOLYMER (SOFT PARTICLE); POLYHYDROXYSTEARIC ACID (2300 MW); XANTHAN GUM; BENTONITE; CETOSTEARYL ALCOHOL; MECASERMIN; NEPIDERMIN; DIMETHICONE; MEDIUM-CHAIN TRIGLYCERIDES; ALANINE; TAURINE; LACTIC ACID; HONEY; PALMITOYL TETRAPEPTIDE-7; SERINE; LECITHIN, SOYBEAN; MALTODEXTRIN; MANNITOL; 1,2-HEXANEDIOL; THREONINE; ISOLEUCINE; FOLIC ACID; CYCLOMETHICONE 5; FIBROBLAST GROWTH FACTOR-1; GLYCINE; CAESALPINIA SPINOSA FRUIT POD; POLYSORBATE 20; BASIC FIBROBLAST GROWTH FACTOR (HUMAN); ACETYL HEXAPEPTIDE-8; ACEGLUTAMIDE; LEUCINE; WATER; HELIANTHUS ANNUUS SPROUT; BUTYLENE GLYCOL; CAPRYLYL GLYCOL; ETHYLHEXYLGLYCERIN; MICA; LYSINE HYDROCHLORIDE; ARGININE; VALINE; DIMETHYLMETHOXY CHROMANYL PALMITATE; CITRIC ACID MONOHYDRATE; FERRIC OXIDE RED

Drug Facts

Active Ingredient:

Zinc Oxide 16%

Purpose Sunscreen

INDICATIONS AND USAGE

Use(s) • helps prevent sunburn • if used as directed with other sun protection measures (see Directions), decreases the risk of skin cancer and early skin aging caused by the sun.

Warnings For external use only.

Do not use on damaged or broken skin.

When using this product keep out of eyes. Rinse with water to remove.

Stop use and ask a doctor if rash occurs.

Keep out of reach of children. If product is swallowed, get medical help or contact a Poison Control Center right away.

DOSAGE AND ADMINISTRATION

Directions • apply liberally and evenly to face 15 minutes before sun exposure • use a water-resistant sunscreen if swimming or sweating • reapply every 2 hours • Sun Protection Measures. Spending time in the sun increases your risk of skin cancer and early skin aging. To decrease this risk, regularly use a sunscreen with a broad-spectrum SPF of 15 or higher and other sun protection measures including: • limit time in the sun, especially from 10 a.m. - 2 p.m. • wear long-sleeve shirts, pants, hat and sunglasses • children under 6 months: Ask a doctor

Other Information Protect this product from excessive heat & direct sun.

INACTIVE INGREDIENT

Inactive Ingredients: Water, Brassica Napus Extract, Dimethicone, Cyclopentasiloxane, Caprylic/Capric Triglyceride, Glycerin, Propanediol, Bentonite, Cetearyl Alcohol, Polyglyceryl-8 Oleate, Sodium Chloride, Peptide-Rich Plasma® (sh-Oligopeptide-2, sh-Polypeptide-1, sh-Polypeptide-9, sh-Polypeptide-11, Acetyl Hexapeptide-8, sh-Oligopeptide-1, Palmitoyl Tripeptide-5, Palmitoyl Tetrapeptide-7, Acetyl Glutamine, Sodium Hyaluronate, Lysine HCL, Alanine, Histidine HCL, Arginine, Serine, Proline, Glutamic Acid, Threonine, Valine, Leucine, Glycine, Isoleucine, Phenylalanine, Taurine), Lactic Acid, Honey, Dimethylmethoxy Chromanyl Palmitate, Hydrolyzed Sodium Hyaluronate, Allantoin, Caesalpinia Spinosa Fruit Pod Extract, Helianthus Annuus (Sunflower) Sprout Extract, Bacillus/Folic Acid Ferment Filtrate Extract, Lecithin, Butylene Glycol, Maltodextrin, Mannitol, Xanthan Gum, Dimethicone/Vinyl Dimethicone Crosspolymer, Caprylyl Glycol, Citric Acid, Polysorbate 20, 1,2-Hexanediol, Polyhydroxystearic Acid, Phenoxyethanol, Ehtylhexylglycerin, Iron Oxides, Mica.